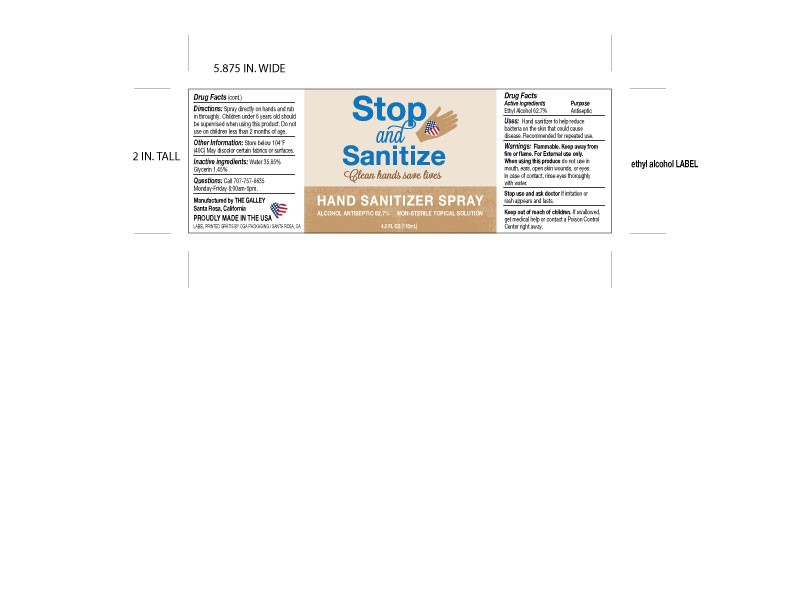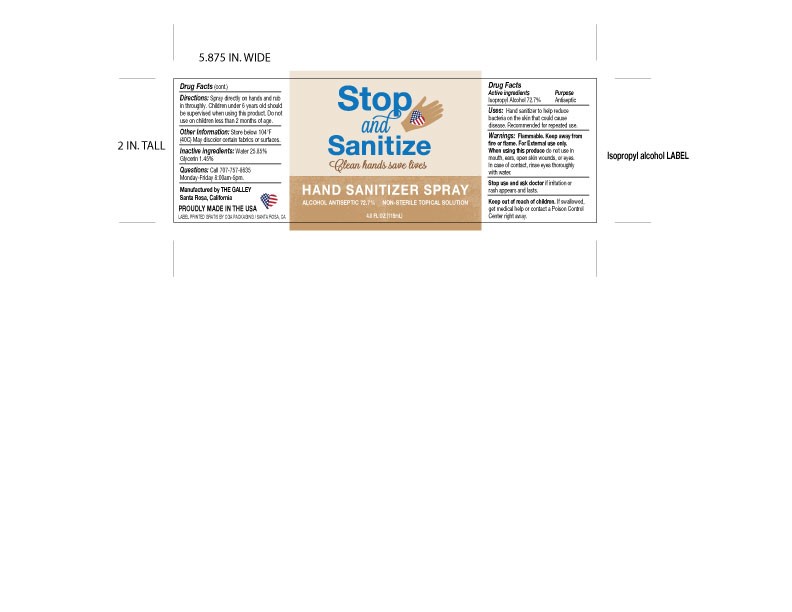 DRUG LABEL: Hand Sanitizer
NDC: 74983-120 | Form: SPRAY
Manufacturer: QVI Inc
Category: otc | Type: HUMAN OTC DRUG LABEL
Date: 20200410

ACTIVE INGREDIENTS: ALCOHOL 80 mL/120 mL
INACTIVE INGREDIENTS: GLYCERIN 1.8 mL/120 mL; WATER 39 mL/120 mL

Hand Sanitizer Spray

Active Ingredient(s)

Alcohol 80% v/v. Purpose: Antiseptic

Purpose

Antiseptic, Hand Sanitizer

Use

Hand Sanitizer to help reduce bacteria that potentially can cause disease. For use when soap and water are not available.

Warnings

Flammable. Keep away from fire or flame. For External use only. When using this product do not use in mouth, ears, open skin wounds, or eyes. In case of contact, rinse eye thoroughly with water.

Do not use

- in children less than 2 months of age
- on open skin wounds
- Ears
- mouth
- eyes

When using this product keep out of eyes, ears, and mouth. In case of contact with eyes, rinse eyes thoroughly with water.
Stop use and ask a doctor if irritation or rash occurs. These may be signs of a serious condition.
Keep out of reach of children. If swallowed, get medical help or contact a Poison Control Center right away.

Stop use and ask a doctor if irritation or rash appears and lasts.

Keep out of reach of children. If swallowed, get medical help or contact a Poison Control Center right away.

Directions

- Spray directly on hands and rub in throughly.
- Children under 6 years old should be supervised when using this product. Do not us on children less than 2 months of age.

Other information

- Store below 104F (40C). May discolor certain fabrics or surfaces.

Inactive ingredients

glycerin, purified water USP

PACKAGE LABEL

120mL NDC:74983-120-02 120 mL NDC:74983-120-02